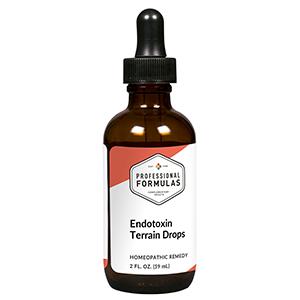 DRUG LABEL: Endotoxin Terrain Drops
NDC: 63083-2143 | Form: LIQUID
Manufacturer: Professional Complementary Health Formulas
Category: homeopathic | Type: HUMAN OTC DRUG LABEL
Date: 20190815

ACTIVE INGREDIENTS: BEEF LUNG 6 [hp_X]/59 mL; HYSSOPUS OFFICINALIS WHOLE 6 [hp_X]/59 mL; ACONITUM NAPELLUS WHOLE 6 [hp_X]/59 mL; ACTIVATED CHARCOAL 6 [hp_X]/59 mL; BEEF LIVER 8 [hp_X]/59 mL; LACHESIS MUTA VENOM 9 [hp_X]/59 mL; SUS SCROFA ADRENAL GLAND 12 [hp_X]/59 mL; ARNICA MONTANA WHOLE 12 [hp_X]/59 mL; BEEF KIDNEY 12 [hp_X]/59 mL; WOOD CREOSOTE 12 [hp_X]/59 mL; BOS TAURUS MESENCHYME 12 [hp_X]/59 mL; CAMPHOR (NATURAL) 12 [hp_X]/59 mL; ANTIMONY POTASSIUM TARTRATE 12 [hp_X]/59 mL; AMARYLLIS BELLADONNA WHOLE 12 [hp_X]/59 mL; BAPTISIA TINCTORIA WHOLE 30 [hp_X]/59 mL; ARSENIC TRIOXIDE 30 [hp_X]/59 mL; CROTALUS HORRIDUS HORRIDUS VENOM 60 [hp_X]/59 mL; MERCURIC CHLORIDE 200 [hp_X]/59 mL; HYDROCHLORIC ACID 200 [hp_X]/59 mL; PHOSPHORIC ACID 200 [hp_X]/59 mL; RANCID BEEF 200 [hp_X]/59 mL
INACTIVE INGREDIENTS: ALCOHOL; WATER

C143

ACTIVE INGREDIENTS

Lung 6X
Thymus 6X
Aconitum napellus 6X, 12X, 30X
Carbo vegetabilis 6X, 30X, 100X
Liver 8X
Lachesis mutus 9X, 30X, 60X
Adrenal cortex 12X
Arnica montana 12X
Kidney 12X
Kreosotum 12X
Mesenchyme 12X
Camphora 12X, 30X
Antimonium tartaricum 12X, 30X, 60X
Belladonna 12X, 30X, 200X
Baptisia tinctoria 30X
Arsenicum album 30X, 60X
Crotalus horridus 60X
Mercurius corrosivus 200X
Muriaticum acidum 200X
Phosphoricum acidum 200X
Pyrogenium 200X

QUESTIONS

Professional Formulas

PO Box 2034 Lake Oswego, OR 97035

INDICATIONS

For the temporary relief of cough, occasional headache, nose or throat irritation, minor body or muscle aches, nausea, or shortness of breath.*

PURPOSE

*Claims based on traditional homeopathic practice, not accepted medical evidence. Not FDA evaluated.

WARNINGS

In case of overdose, get medical help or contact a poison control center right away.

Keep out of the reach of children.

PREGNANCY OR BREAST FEEDING

If pregnant or breastfeeding, ask a healthcare professional before use.

DIRECTIONS

Place drops under tongue 30 minutes before/after meals. Adults and children 12 years and over: Take 10 drops up to 3 times per day. Consult a physician for use in children under 12 years of age.

OTHER INFORMATION

Tamper resistant. If seal is broken, do not use. After opening, close container tightly and store at room temperature away from heat.

INACTIVE INGREDIENTS

20% ethanol, purified water.

LABEL

Est 1985

Professional Formulas

Complementary Health

Endotoxin Terrain Drops

Homeopathic Remedy

2 FL. OZ. (59 mL)